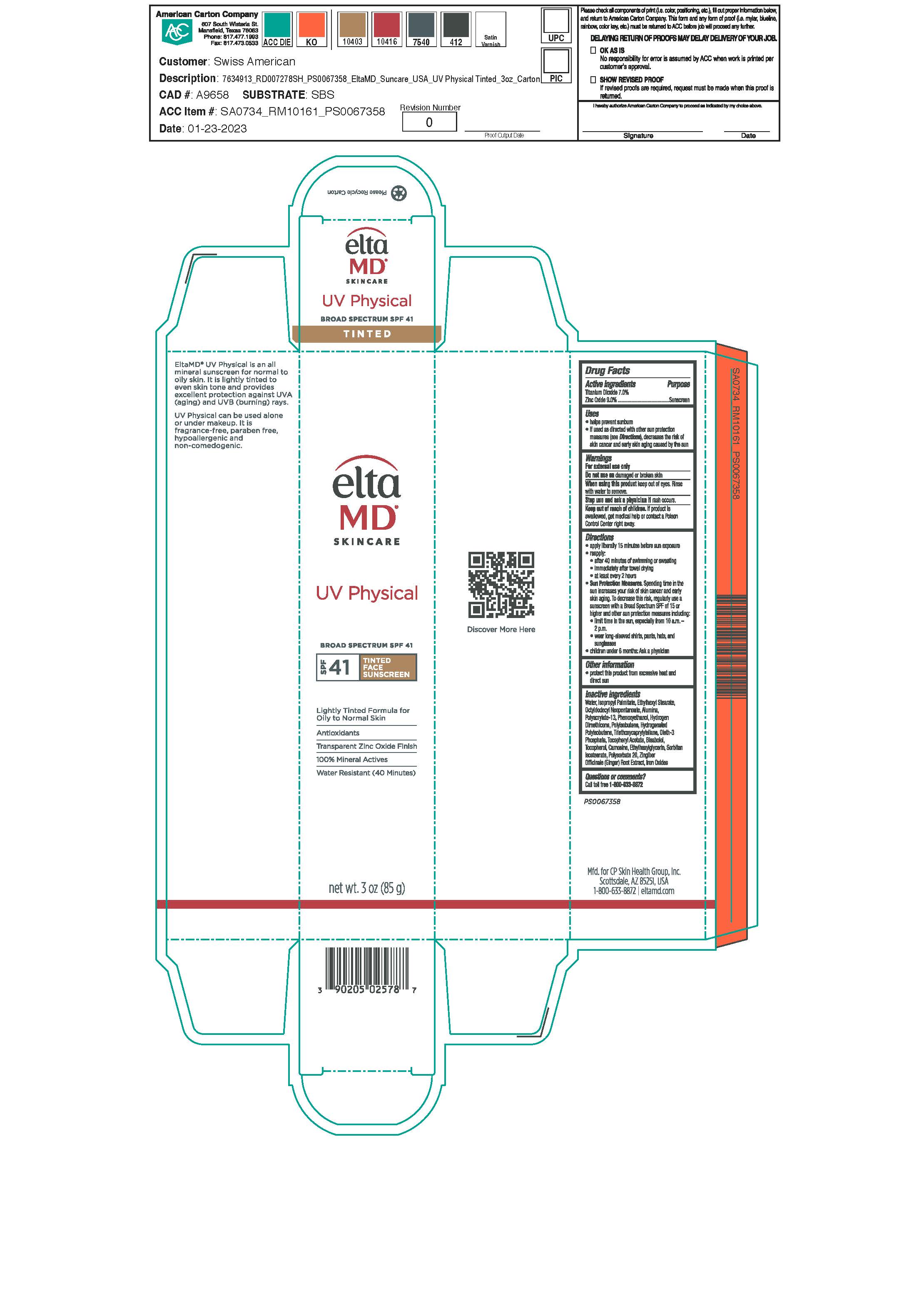 DRUG LABEL: EltaMD UV Physical SPF41
NDC: 72043-2588 | Form: CREAM
Manufacturer: CP Skin Health Group, Inc
Category: otc | Type: HUMAN OTC DRUG LABEL
Date: 20240805

ACTIVE INGREDIENTS: ZINC OXIDE 90 g/1000 g; TITANIUM DIOXIDE 70 g/1000 g
INACTIVE INGREDIENTS: WATER; PHENOXYETHANOL; ETHYLHEXYLGLYCERIN; ISOPROPYL PALMITATE; ETHYLHEXYL STEARATE; OCTYLDODECYL NEOPENTANOATE; .ALPHA.-TOCOPHEROL ACETATE; OLETH-3 PHOSPHATE; PHOSPHORIC ACID; FERRIC OXIDE YELLOW; FERRIC OXIDE RED; FERROSOFERRIC OXIDE; TRIETHOXYCAPRYLYLSILANE; ALUMINUM OXIDE; HYDROGEN DIMETHICONE (13 CST); POLYACRYLATE-13; POLYSORBATE 20; POLYISOBUTYLENE (85000 MW); HYDROGENATED POLYISOBUTENE (1300 MW); TOCOPHEROL; CANOLA OIL; CARNOSINE; ZINGIBER OFFICINALE WHOLE; LEVOMENOL; SODIUM HYDROXIDE; CITRIC ACID MONOHYDRATE; SORBITAN ISOSTEARATE

EltaMD UV Physical SPF41

Warnings

For external use only. Do not use on damaged or broken skin. When using this product keep out of eyes. Rinse with water to remove. Stop use and ask a physician if rash occurs. If product is swallowed get medical help or contact a Poison Control Center right away.

Active Ingredients

Zinc Oxide 9.0% Sunscreen

Titanium Dioxide 7.0% Sunscreen

Purpose

Sunscreen

Indications & Uses:

Helps prevent sunburn. If used as directed with other sun protection measure (See Directions), decreases the risk of skin cancer and early skin aging caused by the sun.

Keep out of reach of children

Directions

Apply liberally 15 minutes before sun exposure. Reapply after 40 minutes of swimming or sweating, immediately after towel drying and at least every 2 hours. Sun Protection Measures: Spending time in the sun increases your risk of skin cancer and early skin aging. To decrease this risk, regularly use a sunscreen with a broad-spectrum SPF of 15 or higher and other sun protection measures including: limit time in the sun, especially from 10 am to 2 pm. Wear long-sleeve shirts, pants, hats, and sunglasses. Children under 6 months: ask a physician.

Other Information

Protect this product from excessive heat and direct sun

Inactive Ingredients

water, isopropyl palmitate, ethylkhexyl stearate, octyldodecyl neopentanoate, alumina, polyacrylate-13, phenoxyethanol, hydrogen dimethicone, polyisobutene, hydrogenated polyisobutene, triehtoxycaprylylsilane, oleth-3 phosphate, tocopheryl acetate, bisabolol, tocopherol, carnosine, ethylhexylglycerin, sorbitan isostearate, polysorbate 20, zingiber officinale (ginger) root extract, iron oxides

Questions or Comments?

Call toll free 1-800-633-8872